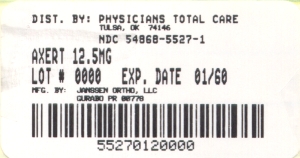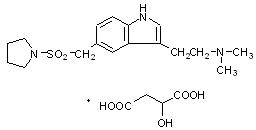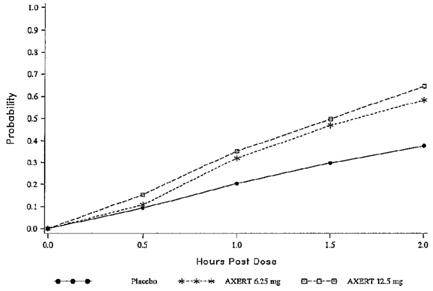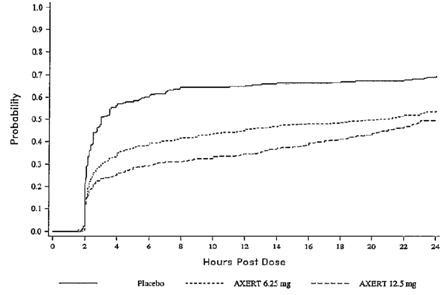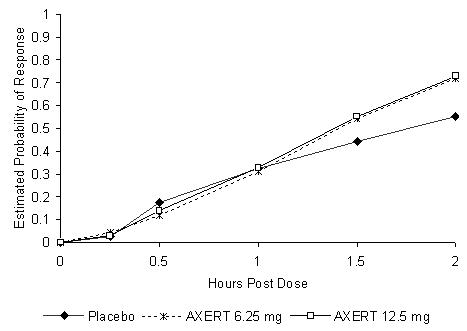 DRUG LABEL: Axert
NDC: 54868-5527 | Form: TABLET, COATED
Manufacturer: Physicians Total Care, Inc.
Category: prescription | Type: HUMAN PRESCRIPTION DRUG LABEL
Date: 20121010

ACTIVE INGREDIENTS: almotriptan malate 12.5 mg/1 1
INACTIVE INGREDIENTS: mannitol; powdered cellulose; sodium starch glycolate type A potato; sodium stearyl fumarate; titanium dioxide; hypromelloses; polyethylene glycols; propylene glycol; ferric oxide red; carnauba wax

HIGHLIGHTS OF PRESCRIBING INFORMATION

These highlights do not include all the information needed to use AXERT® safely and effectively. See full prescribing information for AXERT®.
AXERT (almotriptan malate) Tablets for Oral Use
Initial U.S. Approval: 2001

1 INDICATIONS AND USAGE

AXERT® is a 5HT1B/1D receptor agonist (triptan) indicated for:

- Acute treatment of migraine attacks in adults with a history of migraine with or without aura (1.1)
- Acute treatment of migraine headache pain in adolescents age 12 to 17 years with a history of migraine with or without aura, and who have migraine attacks usually lasting 4 hours or more (1.1)

Important limitations:

- Use only after a clear diagnosis of migraine has been established (1.2)
- In adolescents age 12 to 17 years, efficacy of AXERT® on migraine-associated symptoms was not established (1.2)
- Not intended for the prophylactic therapy of migraine (1.2)
- Not indicated for the treatment of cluster headache (1.2)

2 DOSAGE AND ADMINISTRATION

- Adults and adolescents age 12 to 17 years: 6.25 mg or 12.5 mg single dose; may repeat after 2 hours if headache returns; benefit of second dose in patients who have failed to respond to first dose has not been established; maximum daily dose 25 mg (2.1)
- Patients with hepatic or severe renal impairment: 6.25 mg starting dose; maximum daily dose 12.5 mg (2.2, 2.3)

3 DOSAGE FORMS AND STRENGTHS

Tablets: 6.25 mg and 12.5 mg (3)

4 CONTRAINDICATIONS

- Ischemic heart disease, coronary artery vasospasm, or other significant underlying cardiovascular disease (4.1)
- Cerebrovascular syndromes (e.g., history of stroke or TIA) (4.2)
- Peripheral vascular disease (including ischemic bowel disease) (4.3)
- Uncontrolled hypertension (4.4)
- Do not use AXERT® within 24 hours of an ergotamine-containing, or ergot-type medication, or of another 5-HT1 agonist, e.g., another triptan (4.5, 4.6)
- Hemiplegic or basilar migraine (4.7)
- Known hypersensitivity to AXERT® (4.8)

5 WARNINGS AND PRECAUTIONS

- Serious adverse cardiac events, including acute myocardial infarction and life-threatening disturbances of cardiac rhythm (5.1)
- It is strongly recommended that AXERT® not be given to patients in whom unrecognized coronary artery disease (CAD) is predicted by the presence of risk factors. In very rare cases, serious cardiovascular events have been reported in association with AXERT® use in the absence of known cardiovascular disease. If AXERT® is considered, patients should first have a cardiovascular evaluation. If the evaluation is satisfactory, first dose should take place in a physician's office setting (5.1)
- Sensations of pain, tightness, pressure, and heaviness in the chest, throat, neck, and jaw: generally not associated with myocardial ischemia, but patients with signs or symptoms suggestive of angina should be evaluated for the presence of CAD (5.2)
- Cerebrovascular events, some fatal (5.3)
- Gastrointestinal ischemic events and peripheral vasospastic reactions (e.g., Raynaud's syndrome) (5.4)
- Potentially life-threatening serotonin syndrome, particularly in combination with selective serotonin reuptake inhibitors (SSRIs) or serotonin norepinephrine reuptake inhibitors (SNRIs). Monitor patients for neurologic changes and gastrointestinal symptoms if concomitant treatment is clinically warranted (5.5, 7.3)
- Increase in blood pressure, very rarely associated with significant clinical events (4.4, 5.6)
- Use with caution in patients with a known hypersensitivity to sulfonamides (5.7)

6 ADVERSE REACTIONS

The most common adverse reactions (≥1% and greater than placebo) are:

- In adults: nausea, dry mouth and paresthesia (6.1)
- In adolescents: dizziness, somnolence, headache, paresthesia, nausea and vomiting (6.2)

To report SUSPECTED ADVERSE REACTIONS, contact Ortho-McNeil-Janssen Scientific Affairs Customer Communications Center at 1-800-526-7736 or FDA at 1-800-FDA-1088 or www.fda.gov/medwatch.

7 DRUG INTERACTIONS

- Do not use AXERT® and ergotamine-containing or ergot-type medications within 24 hours of each other (4.5, 7.1)
- Do not use AXERT® and other 5-HT1 agonists (e.g., triptans) within 24 hours of each other (4.6, 7.2)
- SSRI or SNRI: life-threatening serotonin syndrome reported during combined use with triptans (5.5, 7.3)
- Ketoconazole: use single dose of AXERT® 6.25 mg; maximum AXERT® daily dose 12.5 mg (7.4)

8 USE IN SPECIFIC POPULATIONS

- Pregnancy: based on animal data, may cause fetal harm (8.1)
- Nursing mothers: use AXERT® with caution (8.3)
- Pediatric use: AXERT® has not been studied in children under 12 years (8.4)
- Geriatric use: insufficient safety and efficacy data; use with caution, usually starting with the 6.25 mg dose (8.5)
- Hepatic impairment: use single 6.25 mg tablet as a starting dose; maximum daily dose 12.5 mg (2.2, 8.6)
- Severe renal impairment: use single 6.25 mg tablet as a starting dose; maximum daily dose 12.5 mg (2.3, 8.7)

FULL PRESCRIBING INFORMATION

1 INDICATIONS AND USAGE

1.1 Acute Treatment of Migraine Attacks

Adults

AXERT® (almotriptan malate) is indicated for the acute treatment of migraine attacks in patients with a history of migraine with or without aura.

Adolescents Age 12 to 17 Years

AXERT® is indicated for the acute treatment of migraine headache pain in patients with a history of migraine attacks with or without aura usually lasting 4 hours or more (when untreated).

1.2 Important Limitations

AXERT® should only be used where a clear diagnosis of migraine has been established. If a patient has no response for the first migraine attack treated with AXERT®, the diagnosis of migraine should be reconsidered before AXERT® is administered to treat any subsequent attacks.

In adolescents age 12 to 17 years, efficacy of AXERT® on migraine-associated symptoms (nausea, photophobia, and phonophobia) was not established. AXERT® is not intended for the prophylactic therapy of migraine or for use in the management of hemiplegic or basilar migraine [see Contraindications (4.7)].

Safety and effectiveness of AXERT® have not been established for cluster headache which is present in an older, predominantly male population.

2 DOSAGE AND ADMINISTRATION

2.1 Acute Treatment of Migraine Attacks

The recommended dose of AXERT® (almotriptan malate) in adults and adolescents age 12 to 17 years is 6.25 mg to 12.5 mg, with the 12.5 mg dose tending to be a more effective dose in adults. As individuals may vary in their response to different doses of AXERT®, the choice of dose should be made on an individual basis.

If the headache is relieved after the initial AXERT® dose but returns, the dose may be repeated after 2 hours. The effectiveness of a second dose has not been established in placebo-controlled trials. The maximum daily dose should not exceed 25 mg. The safety of treating an average of more than four migraines in a 30-day period has not been established.

2.2 Hepatic Impairment

The recommended starting dose of AXERT® in patients with hepatic impairment is 6.25 mg. The maximum daily dose should not exceed 12.5 mg over a 24-hour period [see Warnings and Precautions (5.8) and Clinical Pharmacology (12.3)].

2.3 Renal Impairment

The recommended starting dose of AXERT® in patients with severe renal impairment is 6.25 mg. The maximum daily dose should not exceed 12.5 mg over a 24-hour period [see Warnings and Precautions (5.8) and Clinical Pharmacology (12.3)].

3 DOSAGE FORMS AND STRENGTHS

AXERT® (almotriptan malate) Tablets are available as white, coated, circular, biconvex tablets in the following dosage strengths:

6.25 mg tablet with red code imprint "2080"

12.5 mg tablet with blue stylized imprint "A."

4 CONTRAINDICATIONS

4.1 Ischemic or Vasospastic Coronary Artery Disease, or Other Significant Underlying Cardiovascular Disease

Do not use AXERT® (almotriptan malate) in patients with ischemic heart disease (angina pectoris, history of myocardial infarction, or documented silent ischemia), or in patients who have symptoms or findings consistent with ischemic heart disease, coronary artery vasospasm, including Prinzmetal's variant angina, or other significant underlying cardiovascular disease [see Warnings and Precautions (5.1)].

4.2 Cerebrovascular Syndromes

Do not use AXERT® in patients with cerebrovascular syndromes including (but not limited to) stroke of any type as well as transient ischemic attacks [see Warnings and Precautions (5.3)].

4.3 Peripheral Vascular Disease

Do not use AXERT® in patients with peripheral vascular disease including (but not limited to) ischemic bowel disease [see Warnings and Precautions (5.4)].

4.4 Uncontrolled Hypertension

Because AXERT® may increase blood pressure, do not use AXERT® in patients with uncontrolled hypertension [see Warnings and Precautions (5.6)].

4.5 Ergotamine-Containing and Ergot-Type Medications

Do not use AXERT® and ergotamine-containing or ergot-derived medications like dihydroergotamine, ergotamine tartrate, or methysergide within 24 hours of each other [see Drug Interactions (7.1)].

4.6 Concomitant Use With 5-HT1 Agonists (e.g., Triptans)

AXERT® and other 5-HT1 agonists (e.g., triptans) should not be administered within 24 hours of each other [see Warnings and Precautions (5.1) and (5.2)].

4.7 Hemiplegic or Basilar Migraine

Do not use AXERT® in patients with hemiplegic or basilar migraine.

4.8 Hypersensitivity

AXERT® is contraindicated in patients with known hypersensitivity to almotriptan or any of its inactive ingredients.

5 WARNINGS AND PRECAUTIONS

5.1 Risk of Myocardial Ischemia and Infarction and Other Adverse Cardiac Events

Cardiac Events and Fatalities with 5-HT1 Agonists

Serious adverse cardiac events, including acute myocardial infarction, have been reported within a few hours following administration of AXERT® (almotriptan malate). Life-threatening disturbances of cardiac rhythm and death have been reported within a few hours following the administration of other triptans. Considering the extent of use of triptans in patients with migraine, the incidence of these events is extremely low.

AXERT® can cause coronary vasospasm; at least one of these events occurred in a patient with no cardiac history and with documented absence of coronary artery disease. Because of the close proximity of the events to use of AXERT®, a causal relationship cannot be excluded. Patients who experience signs or symptoms suggestive of angina following dosing should be evaluated for the presence of coronary artery disease (CAD) or a predisposition to Prinzmetal's variant angina before receiving additional doses of medication, and should be monitored electrocardiographically if dosing is resumed and similar symptoms recur.

Premarketing Experience with AXERT® in Adults

Among the 3865 subjects/patients who received AXERT® in premarketing clinical trials, one patient was hospitalized for observation after a scheduled electrocardiogram (ECG) was found to be abnormal (negative T-waves on the left leads) 48 hours after taking a single 6.25 mg dose of almotriptan. The patient, a 48-year-old female, had previously taken 3 other doses for earlier migraine attacks. Myocardial enzymes at the time of the abnormal ECG were normal. The patient was diagnosed as having had myocardial ischemia and that she had a family history of coronary disease. An ECG performed 2 days later was normal, as was a follow-up coronary angiography. The patient recovered without incident.

Postmarketing Experience with AXERT® in Adults

Serious cardiovascular events have been reported in association with the use of AXERT®. The uncontrolled nature of postmarketing surveillance, however, makes it impossible to definitively determine the proportion of the reported cases that were actually caused by almotriptan or to reliably assess causation in individual cases [see Adverse Reactions (6.3)].

Patients with Documented Coronary Artery Disease

Because of the potential of this class of compound (5-HT1 agonists) to cause coronary vasospasm, AXERT® should not be given to patients with documented ischemic or vasospastic coronary artery disease [see Contraindications (4.1)].

Patients with Risk Factors for CAD

It is strongly recommended that AXERT® not be given to patients in whom unrecognized CAD is predicted by the presence of risk factors (e.g., hypertension, hypercholesterolemia, smoker, obesity, diabetes, strong family history of CAD, female with surgical or physiological menopause, or male over 40 years of age) unless a cardiovascular evaluation provides satisfactory clinical evidence that the patient is reasonably free of coronary artery and ischemic myocardial disease or other significant underlying cardiovascular disease. The sensitivity of cardiac diagnostic procedures to detect cardiovascular disease or predisposition to coronary artery vasospasm is modest, at best. If, during the cardiovascular evaluation, the patient's medical history, electrocardiographic or other investigations reveal findings indicative of, or consistent with, coronary artery vasospasm or myocardial ischemia, AXERT® should not be administered [see Contraindications (4.1)].

For patients with risk factors predictive of CAD, who are determined to have a satisfactory cardiovascular evaluation, it is strongly recommended that administration of the first dose of AXERT® take place in the setting of a physician's office or similar medically staffed and equipped facility unless the patient has previously received AXERT®. Because cardiac ischemia can occur in the absence of clinical symptoms, consideration should be given to obtaining on the first occasion of use an ECG during the interval immediately following AXERT®, in these patients with risk factors. It is recommended that patients who are intermittent long-term users of AXERT® and who have or acquire risk factors predictive of CAD, as described above, undergo periodic interval cardiovascular evaluation as they continue to use AXERT®.

The systematic approach described above is intended to reduce the likelihood that patients with unrecognized cardiovascular disease will be inadvertently exposed to AXERT®. The ability of cardiac diagnostic procedures to detect all cardiovascular diseases or predisposition to coronary artery vasospasm is modest at best. Cardiovascular events associated with triptan treatment have occurred in patients with no cardiac history and with documented absence of coronary artery disease.

5.2 Sensations of Pain, Tightness, Pressure in the Chest and/or Throat, Neck, and Jaw

As with other 5-HT1 agonists, sensations of tightness, pain, pressure, and heaviness in the precordium, throat, neck, and jaw have been reported after treatment with AXERT®. Because 5-HT1 agonists may cause coronary vasospasm, patients who experience signs or symptoms suggestive of angina following dosing should be evaluated for the presence of CAD or a predisposition to Prinzmetal's variant angina before receiving additional doses of medication, and should be monitored electrocardiographically if dosing is resumed and similar symptoms occur. Patients shown to have CAD and those with Prinzmetal's variant angina should not receive 5-HT1 agonists [see Contraindications (4.1) and Warnings and Precautions (5.1)].

5.3 Cerebrovascular Events and Fatalities

Cerebral hemorrhage, subarachnoid hemorrhage, stroke, and other cerebrovascular events have been reported in patients treated with other triptans and some events have resulted in fatalities. In a number of cases, it appeared possible that the cerebrovascular events were primary, the triptan having been administered in the incorrect belief that the symptoms experienced were a consequence of migraine, when they were not. As with other acute migraine therapies, before treating headaches in patients not previously diagnosed as migraineurs and in migraineurs who present with atypical symptoms, care should be taken to exclude other potentially serious neurological conditions. It should be noted that patients with migraine may be at increased risk of certain cerebrovascular events (e.g., stroke, hemorrhage, and transient ischemic attack) [see Contraindications (4.2)].

5.4 Other Vasospasm-Related Events, Including Peripheral Vascular Ischemia and Colonic Ischemia

Triptans, including AXERT®, may cause vasospastic reactions other than coronary artery vasospasm, such as peripheral and gastrointestinal vascular ischemia with abdominal pain and bloody diarrhea. Very rare reports of transient and permanent blindness and significant partial vision loss have been reported with the use of triptans. Visual disorders may also be part of a migraine attack. Patients who experience symptoms or signs suggestive of decreased arterial flow following the use of any triptan, such as ischemic bowel syndrome or Raynaud's syndrome, are candidates for further evaluation [see Contraindications (4.3)].

5.5 Serotonin Syndrome

The development of a potentially life-threatening serotonin syndrome may occur with triptans, including AXERT®, particularly during combined use with selective serotonin reuptake inhibitors (SSRIs) or serotonin norepinephrine reuptake inhibitors (SNRIs). If concomitant treatment with AXERT® and an SSRI (e.g., fluoxetine, paroxetine, sertraline, fluvoxamine, citalopram, escitalopram) or SNRI (e.g., venlafaxine, duloxetine) is clinically warranted, careful observation of the patient is advised, particularly during treatment initiation and dose increases. Serotonin syndrome symptoms may include mental status changes (e.g., agitation, hallucinations, coma), autonomic instability (e.g., tachycardia, labile blood pressure, hyperthermia), neuromuscular aberrations (e.g., hyperreflexia, incoordination) and/or gastrointestinal symptoms (e.g., nausea, vomiting, diarrhea) [See Drug Interactions (7.3)].

5.6 Increases in Blood Pressure

As with other triptans, significant elevations in systemic blood pressure have been reported on rare occasions with AXERT® use in patients with and without a history of hypertension; very rarely these increases in blood pressure have been associated with significant clinical events. AXERT® is contraindicated in patients with uncontrolled hypertension [see Contraindications (4.4)]. In normotensive healthy subjects and patients with hypertension controlled by medication, small, but clinically insignificant, increases in mean systolic (0.21 and 4.87 mm Hg, respectively) and diastolic (1.35 and 0.26 mm Hg, respectively) blood pressure relative to placebo were seen over the first 4 hours after oral administration of 12.5 mg of almotriptan.

An 18% increase in mean pulmonary artery pressure was seen following dosing with another triptan in a study evaluating subjects undergoing cardiac catheterization.

5.7 Hypersensitivity to Sulfonamides

Caution should be exercised when prescribing AXERT® to patients with known hypersensitivity to sulfonamides. The chemical structure of almotriptan contains a sulfonyl group, which is structurally different from a sulfonamide. Cross-sensitivity to almotriptan in patients allergic to sulfonamides has not been systematically evaluated.

5.8 Impaired Hepatic or Renal Function

AXERT® should be administered with caution to patients with diseases that may alter the absorption, metabolism, or excretion of drugs, such as those with impaired hepatic or renal function [see Dosage and Administration (2.2), (2.3) and Clinical Pharmacology (12.3)].

5.9 Binding to Melanin-Containing Tissues

When pigmented rats were given a single oral dose of 5 mg/kg of radiolabeled almotriptan, the elimination half-life of radioactivity from the eye was 22 days. This finding suggests that almotriptan and/or its metabolites may bind to melanin in the eye. Because almotriptan could accumulate in melanin-rich tissues over time, there is the possibility that it could cause toxicity in these tissues with extended use. However, no adverse retinal effects related to treatment with almotriptan were noted in a 52-week toxicity study in dogs given up to 12.5 mg/kg/day (resulting in exposure [AUC] to parent drug approximately 20 times that in humans receiving the maximum recommended human dose of 25 mg/day). Although no systematic monitoring of ophthalmologic function was undertaken in clinical trials, and no specific recommendations for ophthalmologic monitoring are offered, prescribers should be aware of the possibility of long-term ophthalmologic effects.

5.10 Corneal Opacities

Three male dogs (out of a total of 14 treated) in a 52-week toxicity study of oral almotriptan developed slight corneal opacities that were noted after 51 weeks, but not after 25 weeks of treatment. The doses at which this occurred were 2, 5, and 12.5 mg/kg/day. The opacity reversed after a 4-week drug-free period in the affected dog treated with the highest dose. Systemic exposure (plasma AUC) to parent drug at 2 mg/kg/day was approximately 2.5 times the exposure in humans receiving the maximum recommended human daily dose of 25 mg. A no-effect dose was not established.

6 ADVERSE REACTIONS

Serious cardiac reactions, including myocardial infarction, have occurred following the use of AXERT® (almotriptan malate) Tablets. These reactions are extremely rare and most have been reported in patients with risk factors predictive of CAD. Reactions reported in association with triptans have included coronary artery vasospasm, transient myocardial ischemia, myocardial infarction, ventricular tachycardia, and ventricular fibrillation [see Contraindications (4.1) and Warnings and Precautions (5.1)].

The following adverse reactions are discussed in more detail in other sections of the labeling:

Risk of Myocardial Ischemia and Infarction and Other Adverse Cardiac Events [see Warnings and Precautions (5.1)]

Sensations of Pain, Tightness, Pressure in the Chest and/or Throat, Neck, and Jaw [see Warnings and Precautions (5.2)]

Cerebrovascular Events and Fatalities [see Warnings and Precautions (5.3)]

Other Vasospasm-Related Events, Including Peripheral Vascular Ischemia and Colonic Ischemia [see Warnings and Precautions (5.4)]

Serotonin Syndrome [see Warnings and Precautions (5.5)]

Increases in Blood Pressure [see Warnings and Precautions (5.6)]

Adverse events were assessed in controlled clinical trials that included 1840 adult patients who received one or two doses of AXERT® and 386 adult patients who received placebo. The most common adverse reactions during treatment with AXERT® were nausea, somnolence, headache, paresthesia, and dry mouth. In long-term open-label studies where patients were allowed to treat multiple attacks for up to 1 year, 5% (63 out of 1347 patients) withdrew due to adverse experiences.

Adverse events were assessed in controlled clinical trials that included 362 adolescent patients who received AXERT® and 172 adolescent patients who received placebo. The most common adverse reactions during treatment with AXERT® were dizziness, somnolence, headache, paresthesia, nausea, and vomiting. In a long-term, open-label study where patients were allowed to treat multiple attacks for up to 1 year, 2% (10 out of 420 adolescent patients) withdrew due to adverse events.

Because clinical studies are conducted under widely varying conditions, adverse reaction rates observed in the clinical studies of a drug cannot be directly compared to rates in the clinical studies of another drug and may not reflect the rates observed in practice.

6.1 Commonly-Observed Adverse Reactions in Double-Blind, Placebo-Controlled AXERT® Clinical Trials

Adults

Table 1 lists the adverse events that occurred in at least 1% of the adult patients treated with AXERT®, and at an incidence greater than in patients treated with placebo, regardless of drug relationship.

Table 1. Incidence of Adverse Events in Controlled Clinical Trials (Reported in at Least 1% of Adult Patients Treated with AXERT®, and at an Incidence Greater than Placebo)
System/Organ Class Adverse Event | AXERT® 6.25 mg (n=527) % | AXERT® 12.5 mg (n=1313) % | Placebo (n=386) %
Digestive Disorders
Nausea | 1 | 2 | 1
Dry mouth | 1 | 1 | 0.5
Nervous System Disorders
Paresthesia | 1 | 1 | 0.5

The incidence of adverse events in controlled clinical trials was not affected by gender, weight, age, presence of aura, or use of prophylactic medications or oral contraceptives. There were insufficient data to assess the effect of race on the incidence of adverse events.

Adolescents

Table 2 lists the adverse reactions reported by 1% or more of AXERT®-treated adolescents age 12 to 17 years in 1 placebo-controlled, double-blind clinical trial.

Table 2. Adverse Reactions Reported by ≥1% of Adolescent Patients Treated with AXERT® in 1 Placebo-Controlled, Double-Blind Clinical Trial
System/Organ Class Adverse Reaction | AXERT® 6.25 mg (n=180) % | AXERT® 12.5 mg (n=182) % | Placebo (n=172) %
Nervous System Disorders
Dizziness | 4 | 3 | 2
Somnolence | <1 | 5 | 2
Headache | 1 | 2 | 1
Paresthesia | <1 | 1 | <1
Gastrointestinal Disorders
Nausea | 1 | 3 | 0
Vomiting | 2 | 0 | <1

6.2 Other Adverse Reactions Observed in AXERT® Clinical Trials

In the paragraphs that follow, the frequencies of less commonly reported adverse clinical reactions are presented. The reports include adverse reactions in 5 adult controlled studies and 1 adolescent controlled study. Variability associated with adverse reaction reporting, the terminology used to describe adverse reactions, etc., limit the value of the quantitative frequency estimates provided. Reaction frequencies are calculated as the number of patients who used AXERT® and reported a reaction divided by the total number of patients exposed to AXERT® (n=3047, all doses). All reported reactions are included except those already listed in the previous table, those too general to be informative, and those not reasonably associated with the use of the drug. Reactions are further classified within system organ class and enumerated in order of decreasing frequency using the following definitions: frequent adverse reactions are those occurring in 1/100 or more patients, infrequent adverse reactions are those occurring in fewer than 1/100 to 1/1000 patients, and rare adverse reactions are those occurring in fewer than 1/1000 patients.

Body: Frequent: Headache. Infrequent: Abdominal cramp or pain, Asthenia, Chills, Back pain, Chest pain, Neck pain, Fatigue, and Rigid neck. Rare: Fever and Photosensitivity reaction.

Cardiovascular: Infrequent: Vasodilation, Palpitations, and Tachycardia. Rare: Hypertension and Syncope.

Digestive: Infrequent: Diarrhea, Vomiting, Dyspepsia, Gastroenteritis, and Increased thirst. Rare: Colitis, Gastritis, Esophageal reflux, and Increased salivation.

Metabolic: Infrequent: Hyperglycemia and Increased serum creatine phosphokinase. Rare: Increased gamma glutamyl transpeptidase and Hypercholesteremia.

Musculo-Skeletal: Infrequent: Myalgia. Rare: Arthralgia, Arthritis, Myopathy, and Muscle weakness.

Nervous: Frequent: Dizziness and Somnolence. Infrequent: Tremor, Vertigo, Anxiety, Hypoesthesia, Restlessness, CNS stimulation, and Shakiness. Rare: Change in dreams, Impaired concentration, Abnormal coordination, Depressive symptoms, Euphoria, Hyperreflexia, Hypertonia, Nervousness, Neuropathy, Nightmares, Nystagmus, and Insomnia.

Respiratory: Infrequent: Pharyngitis, Rhinitis, Dyspnea, Laryngismus, Sinusitis, and Bronchitis. Rare: Hyperventilation, Laryngitis, Sneezing, and Epistaxis.

Skin: Infrequent: Diaphoresis, Pruritus, and Rash. Rare: Dermatitis and Erythema.

Special Senses: Infrequent: Ear pain and Tinnitus. Rare: Diplopia, Dry eyes, Eye pain, Otitis media, Parosmia, Scotoma, Conjunctivitis, Eye irritation, Hyperacusis, and Taste alteration.

Urogenital: Infrequent: Dysmenorrhea.

6.3 Postmarketing Experience

The following adverse reactions have been identified during postapproval use of AXERT®. Because these reactions are reported voluntarily from a population of uncertain size, it is not always possible to reliably estimate their frequency or establish a causal relationship to drug exposure.

Immune System Disorders: Anaphylactic shock

Psychiatric Disorders: Confusional state, Restlessness

Nervous System Disorders: Hemiplegia, Hypoesthesia, Seizures

Eye Disorders: Blepharospasm

Ear and Labyrinth Disorders: Vertigo

Cardiac Disorders: Acute myocardial infarction, Coronary artery vasospasm, Angina pectoris, Tachycardia

Gastrointestinal Disorders: Abdominal discomfort, Abdominal pain, Abdominal pain upper, Colitis, Hypoesthesia oral, Swollen tongue

Skin and Subcutaneous Tissue Disorders: Angioedema, Cold sweat, Erythema, Hyperhidrosis

Musculoskeletal, Connective Tissue, and Bone Disorders: Arthralgia, Myalgia, Pain in extremity

Reproductive System and Breast Disorders: Breast pain

General Disorders: Malaise, Peripheral coldness.

7 DRUG INTERACTIONS

For additional detailed information on drug interactions, see Clinical Pharmacology, Pharmacokinetics (12.3).

7.1 Ergot-Containing Drugs

These drugs have been reported to cause prolonged vasospastic reactions. Because, in theory, vasospastic effects may be additive, ergotamine-containing or ergot-type medications (like dihydroergotamine, ergotamine tartrate, or methysergide) and AXERT® (almotriptan malate) should not be used within 24 hours of each other [see Contraindications (4.5)].

7.2 5-HT1 Agonists (e.g., Triptans)

Concomitant use of other 5-HT1 agonists (e.g., triptans) within 24 hours of treatment with AXERT® is contraindicated [see Contraindications (4.6)].

7.3 Selective Serotonin Reuptake Inhibitors/Serotonin Norepinephrine Reuptake Inhibitors

Cases of life-threatening serotonin syndrome have been reported during combined use of triptans and selective serotonin reuptake inhibitors (SSRIs) or serotonin norepinephrine reuptake inhibitors (SNRIs) [see Warnings and Precautions (5.5)].

7.4 Ketoconazole and Other Potent CYP3A4 Inhibitors

Co-administration of almotriptan and oral ketoconazole, a potent CYP3A4 inhibitor, resulted in an approximately 60% increase in exposure of almotriptan. Increased exposures to almotriptan may be expected when almotriptan is used concomitantly with other potent CYP3A4 inhibitors.

In patients concomitantly using potent CYP3A4 inhibitors, the recommended starting dose of AXERT® is 6.25 mg. The maximum daily dose should not exceed 12.5 mg within a 24-hour period. Concomitant use of AXERT® and potent CYP3A4 inhibitors should be avoided in patients with renal or hepatic impairment.

8 USE IN SPECIFIC POPULATIONS

8.1 Pregnancy

TERATOGENIC EFFECTS

Pregnancy Category C

In animal studies, almotriptan produced developmental toxicity (increased embryolethality and fetal skeletal variations, and decreased offspring body weight) at doses greater than those used clinically. There are no adequate and well-controlled studies in pregnant women; therefore, AXERT® (almotriptan malate) should be used during pregnancy only if the potential benefit justifies the potential risk to the fetus.

When almotriptan (125, 250, 500, or 1000 mg/kg/day) was administered orally to pregnant rats throughout the period of organogenesis, increased incidences of fetal skeletal variations (decreased ossification) were noted at a dose of 250 mg/kg/day or greater and an increase in embryolethality was seen at the highest dose. The no-effect dose for embryo-fetal developmental toxicity in rats (125 mg/kg/day) is approximately 100 times the maximum recommended human dose (MRHD) of 25 mg/day on a body surface area (mg/m^2) basis. Similar studies in pregnant rabbits conducted with almotriptan (oral doses of 5, 20, or 60 mg/kg/day) demonstrated increases in embryolethality at the highest dose. The no-effect dose for embryo-fetal developmental toxicity in rabbits (20 mg/kg/day) is approximately 15 times the MRHD on a mg/m^2 basis. When almotriptan (25, 100, or 400 mg/kg/day) was administered orally to rats throughout the periods of gestation and lactation, gestation length was increased and litter size and offspring body weight were decreased at the highest dose. The decrease in pup weight persisted throughout lactation. The no-effect dose in this study (100 mg/kg/day) is 40 times the MRHD on a mg/m^2 basis.

8.2 Labor and Delivery

The effect of AXERT® on labor and delivery in humans is unknown.

8.3 Nursing Mothers

It is not known whether almotriptan is excreted in human milk. Because many drugs are excreted in human milk, caution should be exercised when AXERT® is administered to a nursing woman. Levels of almotriptan in rat milk were up to 7 times higher than in rat plasma.

8.4 Pediatric Use

Safety and efficacy of AXERT® in pediatric patients under the age of 12 years have not been established. The pharmacokinetics, efficacy, and safety of AXERT® have been evaluated in adolescent patients, age 12 to 17 years [see Clinical Pharmacology (12.3) and Clinical Studies (14.2)].

In a clinical study, AXERT® 6.25 mg and 12.5 mg were found to be effective for the relief of migraine headache pain in adolescent patients age 12 to 17 years. Efficacy on migraine-associated symptoms (nausea, photophobia, and phonophobia) was not established. The most common adverse reactions (incidence of ≥1%) associated with AXERT® treatment were dizziness, somnolence, headache, paresthesia, nausea, and vomiting [see Adverse Reactions (6.1)]. The safety and tolerability profile of AXERT® treatment in adolescents is similar to the profile observed in adults.

Postmarketing experience with other triptans include a limited number of reports that describe pediatric patients who have experienced clinically serious adverse events that are similar in nature to those reported rarely in adults.

8.5 Geriatric Use

Clinical studies of AXERT® did not include sufficient numbers of subjects age 65 and over to determine whether they respond differently from younger subjects. Clearance of almotriptan was lower in elderly volunteers than in younger individuals, but there were no observed differences in the safety and tolerability between the two populations [see Clinical Pharmacology (12.3)]. In general, dose selection for an elderly patient should be cautious, usually starting at the low dose, reflecting the greater frequency of decreased hepatic, renal, or cardiac function, and of concomitant disease or other drug therapy. The recommended dose of AXERT® for elderly patients with normal renal function for their age is the same as that recommended for younger adults.

8.6 Hepatic Impairment

The recommended starting dose of AXERT® in patients with hepatic impairment is 6.25 mg. The maximum daily dose should not exceed 12.5 mg over a 24-hour period [see Dosage and Administration (2.2) and Clinical Pharmacology (12.3)].

8.7 Renal Impairment

The recommended starting dose of AXERT® in patients with severe renal impairment is 6.25 mg. The maximum daily dose should not exceed 12.5 mg over a 24-hour period [see Dosage and Administration (2.3) and Clinical Pharmacology (12.3)].

10 OVERDOSAGE

10.1 Signs and Symptoms

Patients and volunteers receiving single oral doses of 100 to 150 mg of almotriptan did not experience significant adverse events. Six additional normal volunteers received single oral doses of 200 mg without serious adverse events. During clinical trials with AXERT® (almotriptan malate), one patient ingested 62.5 mg in a 5-hour period and another patient ingested 100 mg in a 38-hour period. Neither patient experienced adverse reactions.

Based on the pharmacology of triptans, hypertension or other more serious cardiovascular symptoms could occur after overdosage.

10.2 Recommended Treatment

Gastrointestinal decontamination (i.e., gastric lavage followed by activated charcoal) should be considered in patients suspected of an overdose with AXERT®. Clinical and electrocardiographic monitoring should be continued for at least 20 hours even if clinical symptoms are not observed.

It is unknown what effect hemodialysis or peritoneal dialysis has on plasma concentrations of almotriptan.

11 DESCRIPTION

AXERT® (almotriptan malate) Tablets contain almotriptan malate, a selective 5-hydroxytryptamine1B/1D (5-HT1B/1D) receptor agonist. Almotriptan malate is chemically designated as 1-[[[3-[2-(Dimethylamino)ethyl]-1H-indol-5-yl]methyl]sulfonyl]pyrrolidine (±)-hydroxybutanedioate (1:1) and its structural formula is:

Its empirical formula is C17H25N3O2S-C4H6O5, representing a molecular weight of 469.56. Almotriptan is a white to slightly yellow crystalline powder that is soluble in water. AXERT® for oral administration contains almotriptan malate equivalent to 6.25 or 12.5 mg of almotriptan. Each compressed tablet contains the following inactive ingredients: mannitol, cellulose, povidone, sodium starch glycolate, sodium stearyl fumarate, titanium dioxide, hypromellose, polyethylene glycol, propylene glycol, iron oxide (6.25 mg only), FD&C Blue No. 2 (12.5 mg only), and carnauba wax.

12 CLINICAL PHARMACOLOGY

12.1 Mechanism of Action

Almotriptan binds with high affinity to 5-HT1D, 5-HT1B, and 5-HT1F receptors. Almotriptan has weak affinity for 5-HT1A and 5-HT7 receptors, but has no significant affinity or pharmacological activity at 5-HT2, 5-HT3, 5-HT4, 5-HT6; alpha or beta adrenergic; adenosine (A1, A2); angiotensin (AT1, AT2); dopamine (D1, D2); endothelin (ETA, ETB); or tachykinin (NK1, NK2, NK3) binding sites.

12.2 Pharmacodynamics

Current theories on the etiology of migraine headache suggest that symptoms are due to local cranial vasodilatation and/or to the release of vasoactive and pro-inflammatory peptides from sensory nerve endings in an activated trigeminal system. The therapeutic activity of almotriptan in migraine can most likely be attributed to agonist effects at 5-HT1B/1D receptors on the extracerebral, intracranial blood vessels that become dilated during a migraine attack and on nerve terminals in the trigeminal system. Activation of these receptors results in cranial vessel constriction, inhibition of neuropeptide release, and reduced transmission in trigeminal pain pathways.

12.3 Pharmacokinetics

Absorption

The absolute bioavailability of almotriptan is about 70%, with peak plasma levels occurring 1 to 3 hours after administration; food does not affect pharmacokinetics.

Distribution

Almotriptan is minimally protein bound (approximately 35%) and the mean apparent volume of distribution is approximately 180 to 200 liters.

Metabolism

Almotriptan is metabolized by two major and one minor pathways. Monoamine oxidase (MAO)-mediated oxidative deamination (approximately 27% of the dose), and cytochrome P450-mediated oxidation (approximately 12% of the dose) are the major routes of metabolism, while flavin monooxygenase is the minor route. MAO-A is responsible for the formation of the indoleacetic acid metabolite, whereas cytochrome P450 (3A4 and 2D6) catalyzes the hydroxylation of the pyrrolidine ring to an intermediate that is further oxidized by aldehyde dehydrogenase to the gamma-aminobutyric acid derivative. Both metabolites are inactive.

Excretion

Almotriptan has a mean half-life of 3 to 4 hours. Almotriptan is eliminated primarily by renal excretion (about 75% of the oral dose), with approximately 40% of an administered dose excreted unchanged in urine. Renal clearance exceeds the glomerular filtration rate by approximately 3-fold, indicating an active mechanism. Approximately 13% of the administered dose is excreted via feces, both unchanged and metabolized.

Drug-Drug Interactions

All drug interaction studies were performed in healthy volunteers using a single 12.5 mg dose of almotriptan and multiple doses of the other drug.

Monoamine Oxidase Inhibitors

Co-administration of almotriptan and moclobemide (150 mg twice daily for 8 days) resulted in a 27% decrease in almotriptan clearance and an increase in Cmax of approximately 6%. No dose adjustment is necessary.

Propranolol

Co-administration of almotriptan and propranolol (80 mg twice daily for 7 days) resulted in no significant changes in the pharmacokinetics of almotriptan.

Fluoxetine

Co-administration of almotriptan and fluoxetine (60 mg daily for 8 days), a potent inhibitor of CYP2D6, had no effect on almotriptan clearance, but maximal concentrations of almotriptan were increased 18%. This difference is not clinically significant.

Verapamil

Co-administration of almotriptan and verapamil (120 mg sustained-release tablets twice daily for 7 days), an inhibitor of CYP3A4, resulted in a 20% increase in the area under the plasma concentration-time curve, and in a 24% increase in maximal plasma concentrations of almotriptan. Neither of these changes is clinically significant. No dose adjustment is necessary.

Ketoconazole and other Potent CYP3A4 Inhibitors

Co-administration of almotriptan and ketoconazole, a potent CYP3A4 inhibitor, resulted in an approximately 60% increase in exposure of almotriptan. Increased exposures to almotriptan may be expected when almotriptan is used with other potent CYP3A4 inhibitors.

Special Populations

Geriatric

Renal and total clearance, and amount of drug excreted in the urine, were lower in elderly healthy volunteers (age 65 to 76 years) than in younger healthy volunteers (age 19 to 34 years), resulting in longer terminal half-life (3.7 hours vs. 3.2 hours) and a 25% higher area under the plasma concentration-time curve in the elderly subjects. The differences, however, do not appear to be clinically significant.

Pediatric

A pharmacokinetics study of almotriptan was conducted in adolescents (12 to 17 years) and adults (18 to 55 years) with or without a history of migraine. No differences were observed in the rate or extent of absorption of almotriptan in adolescents compared with adults.

Gender

No significant gender differences were observed in pharmacokinetic parameters.

Race

No significant differences were observed in pharmacokinetic parameters between Caucasian and African-American volunteers.

Hepatic Impairment

The pharmacokinetics of almotriptan have not been assessed in patients with hepatic impairment. Based on the known mechanisms of clearance of almotriptan, the maximum decrease expected in almotriptan clearance due to hepatic impairment would be 60% [see Dosage and Administration (2.2)].

Renal Impairment

The clearance of almotriptan was approximately 65% lower in patients with severe renal impairment (Cl/F=19.8 L/hour; creatinine clearance between 10 and 30 mL/min) and approximately 40% lower in patients with moderate renal impairment (Cl/F=34.2 L/hour; creatinine clearance between 31 and 71 mL/min) than in healthy volunteers (Cl/F=57 L/hour). Maximal plasma concentrations of almotriptan increased by approximately 80% in these patients [see Dosage and Administration (2.3)].

13 NONCLINICAL TOXICOLOGY

13.1 Carcinogenesis, Mutagenesis, Impairment of Fertility

Carcinogenesis

Almotriptan was administered to mice and rats for up to 103–104 weeks at oral doses up to 250 mg/kg/day and 75 mg/kg/day, respectively. These doses were associated with plasma exposures (AUC) to parent drug that were approximately 40 and 80 times, in mice and rats respectively, the plasma AUC in humans at the maximum recommended human dose (MRHD) of 25 mg/day. Because of high mortality rates in both studies, which reached statistical significance in high-dose female mice, all female rats, all male mice, and high-dose female mice were terminated between weeks 96 and 98. There was no increase in tumors related to almotriptan administration.

Mutagenesis

Almotriptan was not mutagenic in two in vitro gene mutation assays, the Ames test, and the mouse lymphoma tk assay. Almotriptan was not clastogenic in an in vivo mouse micronucleus assay.

Impairment of Fertility

When male and female rats received almotriptan (25, 100, or 400 mg/kg/day) orally prior to and during mating and gestation, prolongation of the estrous cycle was observed at the mid-dose and greater, and fertility was impaired at the highest dose. Subsequent mating of treated with untreated animals indicated that the decrease in fertility was due to an effect on females. The no-effect dose for reproductive toxicity in rats (25 mg/kg/day) is approximately 10 times the MRHD on a mg/m^2 basis.

14 CLINICAL STUDIES

14.1 Adults

The efficacy of AXERT® (almotriptan malate) was established in three multi-center, randomized, double-blind, placebo-controlled European trials. Patients enrolled in these studies were primarily female (86%) and Caucasian (more than 98%), with a mean age of 41 years (range of 18 to 72). Patients were instructed to treat a moderate to severe migraine headache. Two hours after taking one dose of study medication, patients evaluated their headache pain. If the pain had not decreased in severity to mild or no pain, the patient was allowed to take an escape medication. If the pain had decreased to mild or no pain at 2 hours but subsequently increased in severity between 2 and 24 hours, it was considered a relapse and the patient was instructed to take a second dose of study medication. Associated symptoms of nausea, vomiting, photophobia, and phonophobia were also evaluated.

In these studies, the percentage of patients achieving a response (mild or no pain) 2 hours after treatment was significantly greater in patients who received either AXERT® 6.25 mg or 12.5 mg, compared with those who received placebo. A higher percentage of patients reported pain relief after treatment with the 12.5 mg dose than with the 6.25 mg dose. Doses greater than 12.5 mg did not lead to a significantly better response. These results are summarized in Table 3.

Table 3. Response Rates 2 Hours Following Treatment of Initial Headache in Adults
 | Placebo | AXERT® 6.25 mg | AXERT® 12.5 mg
Study 1 | 33.8% (n = 80) | 55.4% [p value 0.002 in comparison with placebo] (n = 166) | 58.5% [p value <0.001 in comparison with placebo] (n = 164)
Study 2 | 40.0% (n = 95) | --- | 57.1% [p value 0.008 in comparison with placebo] (n =175)
Study 3 | 33.0% (n = 176) | 55.6% (n = 360) | 64.9% (n = 370)

The estimated probability of achieving pain relief within 2 hours following initial treatment with AXERT® in adults is shown in Figure 1.

Figure 1. Estimated Probability of Achieving an Initial Headache Response (Mild or no Pain) in 2 Hours in Adults

This Kaplan-Meier plot is based on data obtained in the three placebo-controlled clinical trials that provided evidence of efficacy (Studies 1, 2, and 3). Patients not achieving pain relief by 2 hours were censored at 2 hours.

For patients with migraine-associated photophobia, phonophobia, nausea, and vomiting at baseline, there was a decreased incidence of these symptoms following administration of AXERT® compared with placebo.

Two to 24 hours following the initial dose of study medication, patients were allowed to take an escape medication or a second dose of study medication for pain response. The estimated probability of patients taking escape medication or a second dose of study medication over the 24 hours following the initial dose of study medication is shown in Figure 2.

Figure 2. Estimated Probability of Adult Patients Taking Escape Medication or a Second Dose of Study Medication Over the 24 Hours Following the Initial Dose of Study Treatment

This Kaplan-Meier plot is based on data obtained in the three placebo-controlled trials that provided evidence of efficacy (Studies 1, 2, and 3). Patients not using additional treatment were censored at 24 hours. Remedication was not allowed within 2 hours after the initial dose of AXERT®.

The efficacy of AXERT® was unaffected by the presence of aura; by gender, weight, or age of the patient; or by concomitant use of common migraine prophylactic drugs (e.g., beta-blockers, calcium channel blockers, and tricyclic antidepressants); or oral contraceptives. There were insufficient data to assess the effect of race on efficacy.

14.2 Adolescents Age 12 to 17 Years

The efficacy of AXERT® in adolescent patients age 12 to 17 years was evaluated in a double-blind, randomized, placebo-controlled study. Patients enrolled in that study had at least a 1-year history of migraine attacks with or without aura usually lasting 4 hours or more (when untreated). Patients enrolled in the study were primarily females (60%) and Caucasian (75%), while 15% of patients were black, and 10% were of other races. Patients were instructed to treat a moderate to severe migraine headache. Two hours after taking one dose of study medication, patients evaluated their headache pain. Associated symptoms of nausea, photophobia, and phonophobia were also evaluated.

In this study, the percentage of patients achieving a pain relief response (mild or no pain) 2 hours after treatment was statistically significantly greater in patients who received AXERT® 6.25 mg or 12.5 mg compared with those who received placebo. There was no additional benefit on pain relief provided by the 12.5 mg dose. The 2-hour pain relief results are summarized in Table 4.

Table 4. Response Rates 2 Hours Following Treatment of Initial Headache in Adolescents Age 12 to 17 Years
 | Placebo | AXERT® 6.25 mg | AXERT® 12.5 mg
Study 1 | 55.3% (n/N = 94/170) | 71.8% [p value 0.001 in comparison with placebo] (n/N = 127/177) | 72.9% [p value <0.001 in comparison with placebo] (n/N = 132/181)

The estimated probability of achieving pain relief within 2 hours following initial treatment with AXERT® in adolescents age 12 to 17 years is shown in Figure 3.

Figure 3. Estimated Probability of Achieving an Initial Headache Response (Mild or no Pain) in 2 Hours in the Adolescent Study

The prevalence of the migraine-associated symptoms (nausea, photophobia, and phonophobia) at 2 hours after taking the dose was not significantly different between patients who received AXERT® 6.25 mg or 12.5 mg and those who received placebo.

16 HOW SUPPLIED/STORAGE AND HANDLING

AXERT® (almotriptan malate) Tablets are available as follows:

12.5 mg: White, coated, circular, biconvex tablets with blue stylized imprint "A."

Unit Dose (aluminum blister pack)
12 tablets NDC 54868-5527-1

STORAGE AND HANDLING

Store at 25°C (77°F); excursions permitted to 15°–30°C (59°–86°F) [see USP Controlled Room Temperature].

17 PATIENT COUNSELING INFORMATION

See FDA-Approved Patient Labeling

17.1 Patient Information Leaflet

Inform patients that Patient Information labeling is available as a separate leaflet. Advise the patient to read this information and assist them in understanding its contents. Provide the patient the opportunity to discuss the contents of the Patient Information and answer any questions they may have. The complete text of the Patient Information is attached to the package insert.

17.2 Risk of Myocardial Ischemia and/or Infarction, Other Adverse Cardiac Events, Other Vasospasm-Related Events, and Cerebrovascular Events

Inform patients that AXERT® (almotriptan malate) may cause serious cardiovascular side effects such as myocardial infarction or stroke, which may result in hospitalization and even death. Although serious cardiovascular events can occur without warning symptoms, patients should be alert for the signs and symptoms of chest pain, shortness of breath, weakness, or slurring of speech, and should ask for medical advice when observing any indicative signs or symptoms. Apprise the patient of the importance of this follow-up [see Warnings and Precautions (5.1), (5.2), (5.3), and (5.4)].

17.3 Serotonin Syndrome

Caution patients about the risk of serotonin syndrome with the use of AXERT® or other triptans, particularly during combined use with selective serotonin reuptake inhibitors (SSRIs) or serotonin norepinephrine reuptake inhibitors (SNRIs) [see Warnings and Precautions (5.5)].

17.4 Pregnancy

Advise patients to notify their physician if they become pregnant during treatment or intend to become pregnant [see Use in Specific Populations (8.1)].

17.5 Nursing Mothers

Advise patients to notify their physician if they are breastfeeding or plan to breastfeed [see Use in Specific Populations (8.3)].

17.6 Drug Interactions

Advise patients to talk with their physician or pharmacist before taking any new medicines, including prescription and non-prescription drugs and supplements [see Contraindications (4.5) and (4.6) and Drug-Drug Interactions (7)].

17.7 Ability to Operate Machinery or Vehicles

Counsel patients that AXERT® may cause dizziness, somnolence, visual disturbances, and other CNS symptoms that can interfere with driving or operating machinery. Accordingly, advise the patient not to drive, operate complex machinery, or engage in other hazardous activities until they have gained sufficient experience with AXERT® to gauge whether it affects their mental or visual performance adversely.

17.8 Hypersensitivity

Inform patients to tell their physician if they develop a rash, itching, or breathing difficulties after taking AXERT® [see Warnings and Precautions (5.7)].

17.9 FDA-Approved Patient Labeling

See attached.

AXERT® Tablets are manufactured by:
Janssen-Ortho, LLC
Gurabo, Puerto Rico 00778

(Ortho-McNeil Neurologics logo)

AXERT® Tablets are manufactured for:
Ortho-McNeil Neurologics,
Division of Ortho-McNeil-Janssen Pharmaceuticals, Inc.
Titusville, NJ 08560

Licensed from: Almirall, S.A.
U.S. Patent No. 5,565,447

Revised April 2011
Insert new code

Additional barcode labeling by:
Physicians Total Care, Inc.
Tulsa, Oklahoma 74146

PATIENT LABELING

AXERT® (AX-ert)
(almotriptan malate) TABLETS

Please read this information before you start taking AXERT® (almotriptan malate) Tablets. Also, read this leaflet each time you renew your prescription just in case anything has changed. Remember, this leaflet does not take the place of careful discussions with your doctor. You and your doctor should discuss AXERT® when you start taking your medication and at regular checkups.

What is AXERT® and what is it used for?

AXERT® is a medication used to treat migraine attacks in adults and adolescents age 12 to 17 years. AXERT® is a member of a class of drugs called selective serotonin receptor agonists.

Use AXERT® only for a migraine attack. Do not use AXERT® to treat headaches that might be caused by other conditions. Tell your doctor about your symptoms. Your doctor will decide if you have migraine.

There is more information about migraine at the end of this leaflet.

Who should not take AXERT®? [The brands listed are the trademarks of their respective owners and are not the trademarks of Ortho-McNeil-Janssen Pharmaceuticals, Inc.]

Do not take AXERT® if you:

- have ever had heart disease.
- have uncontrolled high blood pressure.
- have hemiplegic or basilar migraine. If you are not sure, ask your doctor.
- have taken another serotonin receptor agonist (e.g., another triptan) in the last 24 hours. These include naratriptan (AMERGE®), rizatriptan (MAXALT®), sumatriptan (IMITREX®, TREXIMET®), or zolmitriptan (ZOMIG®).
- have taken ergotamine-type medicines in the last 24 hours. These include ergotamine (BELLERGAL-S®, CAFERGOT®, ERGOMAR®, WIGRAINE®), dihydroergotamine (D.H.E. 45®), or methysergide (SANSERT®).
- had an allergic reaction to AXERT® or any of its ingredients. The active ingredient is almotriptan malate. Ask your doctor or pharmacist about inactive ingredients.

Tell your doctor if you take:

- monoamine oxidase (MAO) inhibitors, such as phenelzine sulfate (NARDIL®) or tranylcypromine sulfate (PARNATE®) for depression or another condition, or if it has been less than two weeks since you stopped taking an MAO inhibitor.
- ketoconazole (NIZORAL®), itraconazole (SPORANOX®), ritonavir (NORVIR®), or erythromycin (EMYCIN®), or if it has been less than one week since you stopped taking one of these drugs.
- selective serotonin reuptake inhibitors (SSRIs) or serotonin norepinephrine reuptake inhibitors (SNRIs), two types of drugs for depression or other disorders. Common SSRIs are CELEXA® (citalopram HBr), LEXAPRO® (escitalopram oxalate), PAXIL® (paroxetine), PROZAC®/SARAFEM® (fluoxetine), SYMBYAX® (olanzapine/fluoxetine), ZOLOFT® (sertraline), and fluvoxamine. Common SNRIs are CYMBALTA® (duloxetine) and EFFEXOR® (venlafaxine).

These medicines may affect how AXERT® works, or AXERT® may affect how these medicines work.

To help your doctor decide if AXERT® is right for you or if you need to be checked while taking AXERT®, tell your doctor about any:

- past or present medical problems.
- past or present high blood pressure, chest pain, shortness of breath, or heart disease.
- liver or kidney problems.
- risk factors for heart disease, such as:
  - high blood pressure
  - diabetes
  - high cholesterol
  - overweight
  - smoking
  - family members with heart disease
  - you are past menopause
  - you are a male over 40 years old.
- allergic reactions to sulfonamides, also known as sulfa drugs (ask your doctor if you are not sure what sulfonamide drugs are).
- medicines you take or plan to take, including prescription and non-prescription medicines and herbal supplements. Be sure to include medicines you normally take for a migraine.

Talk to your doctor about using AXERT® if you are pregnant, planning to become pregnant, or breastfeeding.

How should I take AXERT®?

- When you have a migraine headache, take your medicine as directed by your doctor.
- If your headache comes back after your first dose, you may take a second dose 2 hours or more after the first dose. If your pain continues after the first dose, do not take a second dose without first checking with your doctor.
- Do not take more than two AXERT® Tablets in a 24-hour period.
- If you take too much medicine, contact your doctor, hospital emergency department, or poison control center right away.

What should I avoid while taking AXERT®?

Check with your doctor before you take any new medicines, including prescription and non-prescription medicines and supplements. There are some medicines that you should not take during the period 24 hours before and 24 hours after taking AXERT®. Some of them are listed in the section "Who should not take AXERT?"

What are the possible side effects of AXERT®?

The side effects are usually mild and do not last long. The following is not a complete list of side effects. Ask your doctor to tell you about the other side effects.

The most common side effects in adults are:

- Nausea
- Sleepiness
- Tingling or burning feeling (paresthesia)
- Headache
- Dry mouth

The most common side effects in adolescents are:

- Dizziness
- Sleepiness
- Nausea
- Headache
- Tingling or burning feeling (paresthesia)
- Vomiting

If you experience sleepiness, you should evaluate your ability to perform complex tasks, such as driving or operating heavy machinery.

Tell your doctor about any other symptoms that you develop while taking AXERT®. If the symptoms continue or worsen, get medical help right away. Also, tell your doctor if you develop a rash or itching after taking AXERT®. You may be allergic to the medicine.

In very rare cases, patients taking this class of medicines experience serious heart problems, stroke, or increased blood pressure. Extremely rarely, patients have died. Therefore, tell your doctor right away if you feel tightness, pain, pressure, or heaviness in your chest, throat, neck, or jaw after taking AXERT®. Do not take AXERT® again until your doctor has checked you.

Some people may have a reaction called serotonin syndrome, which can be life-threatening, when they use AXERT®. In particular, this reaction may occur when they use AXERT® together with certain types of antidepressants known as SSRIs or SNRIs. Symptoms may include mental changes (hallucinations, agitation, or coma), fast heartbeat, changes in blood pressure, high body temperature or sweating, tight muscles, trouble walking, nausea, vomiting, or diarrhea. Call your doctor immediately if you have any of these symptoms after taking AXERT®.

This is not a complete list of side effects. Talk to your doctor if you develop any symptoms that concern you.

What to do in case of an overdose?

Call your doctor or poison control center or go to the ER.

What is a migraine and how does it differ from other headaches?

A migraine is an intense, throbbing, typically one-sided headache. It often includes nausea, vomiting, sensitivity to light, and sensitivity to sound. The pain and symptoms from a migraine headache may be worse than the pain and symptoms of a common headache.

Some people have visual symptoms before the headache, such as flashing lights or wavy lines, called an aura.

Migraine attacks typically last for hours or, rarely, for more than a day. They can return often. The strength and frequency of migraine attacks may vary.

Based on your symptoms, your doctor will decide whether you have a migraine.

Migraine headaches tend to occur in members of the same family. Both men and women get migraines, but it is more common in women.

What may trigger a migraine attack?

Certain things may trigger migraine attacks in some people. Some of these triggers are:

- certain foods or drinks, such as cheese, chocolate, citrus fruit (oranges, grapefruit, lemons, limes, and others), caffeine, and alcohol.
- stress.
- a change in behavior, such as too much or too little sleep, missing a meal, or a change in diet.
- hormone changes in women, such as during monthly menstrual periods.

You may be able to prevent migraine attacks or make them come less often if you understand what triggers your attacks. Keeping a headache diary may help you identify and monitor the possible triggers that cause your migraine. Once you identify the triggers, you and your doctor can change your lifestyle to avoid those triggers.

How does AXERT® work during a migraine attack?

Treatment with AXERT®:

- reduces swelling of blood vessels surrounding the brain. This swelling is associated with the headache pain of a migraine attack.
- blocks the release of substances from nerve endings that cause more pain and other symptoms of migraine.
- interrupts the sending of specific pain signals to your brain.

It is thought that each of these actions contributes to relief of your symptoms by AXERT®.

How should I store AXERT®?

Keep your medicine in a safe place where children cannot reach it. It may be harmful to children. Store your medicine away from heat, light, or moisture at a controlled room temperature. If your medicine has expired, throw it away as instructed. If your doctor decides to stop your treatment, do not keep any leftover medicine unless your doctor tells you to do so. Throw away your medicine as instructed. Be sure that discarded tablets are out of the reach of children.

General advice about prescription medicines

Medicines are sometimes prescribed for conditions that are not mentioned in patient information leaflets. Do not use AXERT® for a condition for which it was not prescribed. Do not give AXERT® to other people even if they have the same symptoms you have. People may be harmed if they take medicines that have not been prescribed for them.

This leaflet provides a summary of information about AXERT®. If you have any questions or concerns about either AXERT® or migraines, talk to your doctor. In addition, talk to your pharmacist or other healthcare provider.

AXERT® Tablets are manufactured by:
Janssen-Ortho, LLC
Gurabo, Puerto Rico 00778

AXERT® Tablets are manufactured for:
Ortho-McNeil Neurologics,
Division of Ortho-McNeil-Janssen Pharmaceuticals, Inc.
Titusville, NJ 08560

Licensed from: Almirall, S.A.
U.S.Patent No. 5,565,447

Revised April 2011

PACKAGE LABEL

PRINCIPAL DISPLAY PANEL - 12.5 mg Tablet Carton

NDC 54868-5527-1

Axert®
(almotriptan malate) Tablets

equivalent to
12.5 mg
almotriptan

12 tablets

Rx only